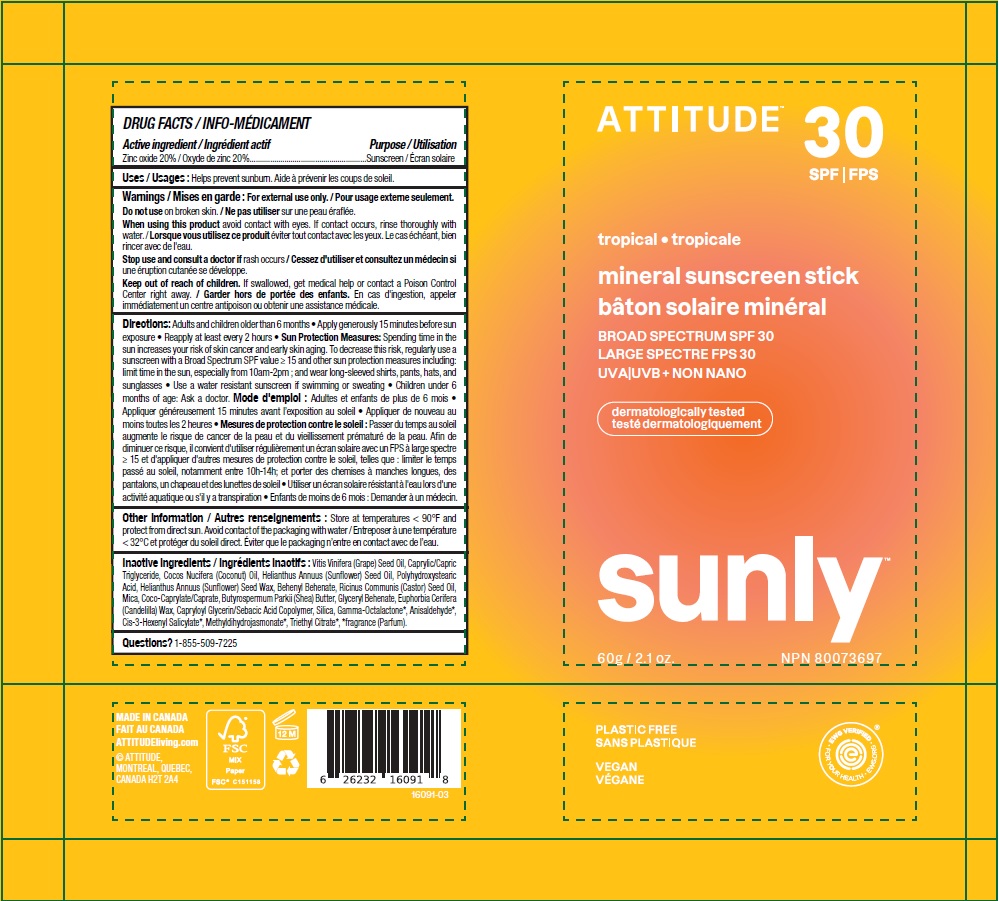 DRUG LABEL: ATTITUDE Sunly Mineral Sunscreen Stick Tropical SPF 30
NDC: 61649-091 | Form: STICK
Manufacturer: 9055-7588 Quebec Inc. DBA Attitude
Category: otc | Type: HUMAN OTC DRUG LABEL
Date: 20241216

ACTIVE INGREDIENTS: ZINC OXIDE 20 g/100 g
INACTIVE INGREDIENTS: COCONUT OIL; GRAPE SEED OIL; GLYCERYL MONOBEHENATE; HELIANTHUS ANNUUS SEED WAX; P-ANISALDEHYDE; .GAMMA.-OCTALACTONE; METHYL DIHYDROJASMONATE (SYNTHETIC); CAPRYLOYL GLYCERIN/SEBACIC ACID COPOLYMER (2000 MPA.S); CANDELILLA WAX; POLYHYDROXYSTEARIC ACID (2300 MW); SHEA BUTTER; MEDIUM-CHAIN TRIGLYCERIDES; SILICON DIOXIDE; TRIETHYL CITRATE; COCO-CAPRYLATE/CAPRATE; BEHENYL BEHENATE; MICA; 3-HEXENYL SALICYLATE, CIS-; CASTOR OIL; SUNFLOWER OIL

ATTITUDE Sunly Mineral Sunscreen Stick - Tropical - SPF 30

DRUG FACTS

ACTIVE INGREDIENT

Zinc oxide (20 %)

PURPOSE

Sunscreen

INDICATIONS AND USAGE

Helps prevent sunburn.

WARNINGS

For external use only.

Do not use on broken skin.

When using this product avoid contact with eyes. If contact occurs, rinse thoroughly with water.

Keep out of reach of children. If swallowed, get medical help or contact a Poison Control Center right away.

Stop use and consult a doctor if rash occurs.

DOSAGE AND ADMINISTRATION

Adults and children older than 6 months.

- Apply generously 15 minutes before sun exposure.
- Reapply at least every 2 hours.
- Sun Protection Measures: Spending time in the sun increases your risk of skin cancer and early aging. To decrease this risk, regularly use a sunscreen with a Broad Spectrum SPFvalue of 15 or higher and other sun protection measures including: limit time in the sun, especially from 10am-2pm; and wear long-sleeved shirts, pants, hats and sunglasses.
- Use a water resistant sunscreen if swimming or sweating.
- Children under 6 months of age: Ask a doctor.

STORAGE AND HANDLING

Store at temperatures < 90F and protect from direct sun. Avoid contact of packaging with water.

INACTIVE INGREDIENT

Vitis Vinifera (Grape) Seed Oil, Caprylic/Capric Triglyceride, Cocos Nucifera (Coconut) Oil, Helianthus Annuus (Sunflower) Seed Oil, Polyhydroxystearic Acid, Helianthus Annuus (Sunflower) Seed Wax, Behenyl Behenate, Ricinus Communis (Castor) Seed Oil, Mica, Coco-Caprylate/Caprate, Butyrospermum Parkii (Shea) Butter, Glyceryl Behenate, Euphorbia Cerifera (Candelilla) Wax, Capryloyl Glycerin/Sebacic Acid Copolymer, Silica, Gamma-Octalactone*, Anisaldehyde*, Cis-3-Hexenyl Salicylate*, Methyldihydrojasmonate*, Triethyl Citrate*, *fragrance (Parfum).

Questions ? 1-855-509-7225

PACKAGE LABEL

ATTITUDE

SPF 30

tropical

mineral sunscreen stick

BROAD SPECTRUM SPF 30

UVA UVB + NON NANO

SUNLY Plastic Free Suncare

60 g / 2.1 oz.

NPN 80073697

Vegan

EWG Verified

Ocean Lovers

Plastic Free

Dermatologically tested